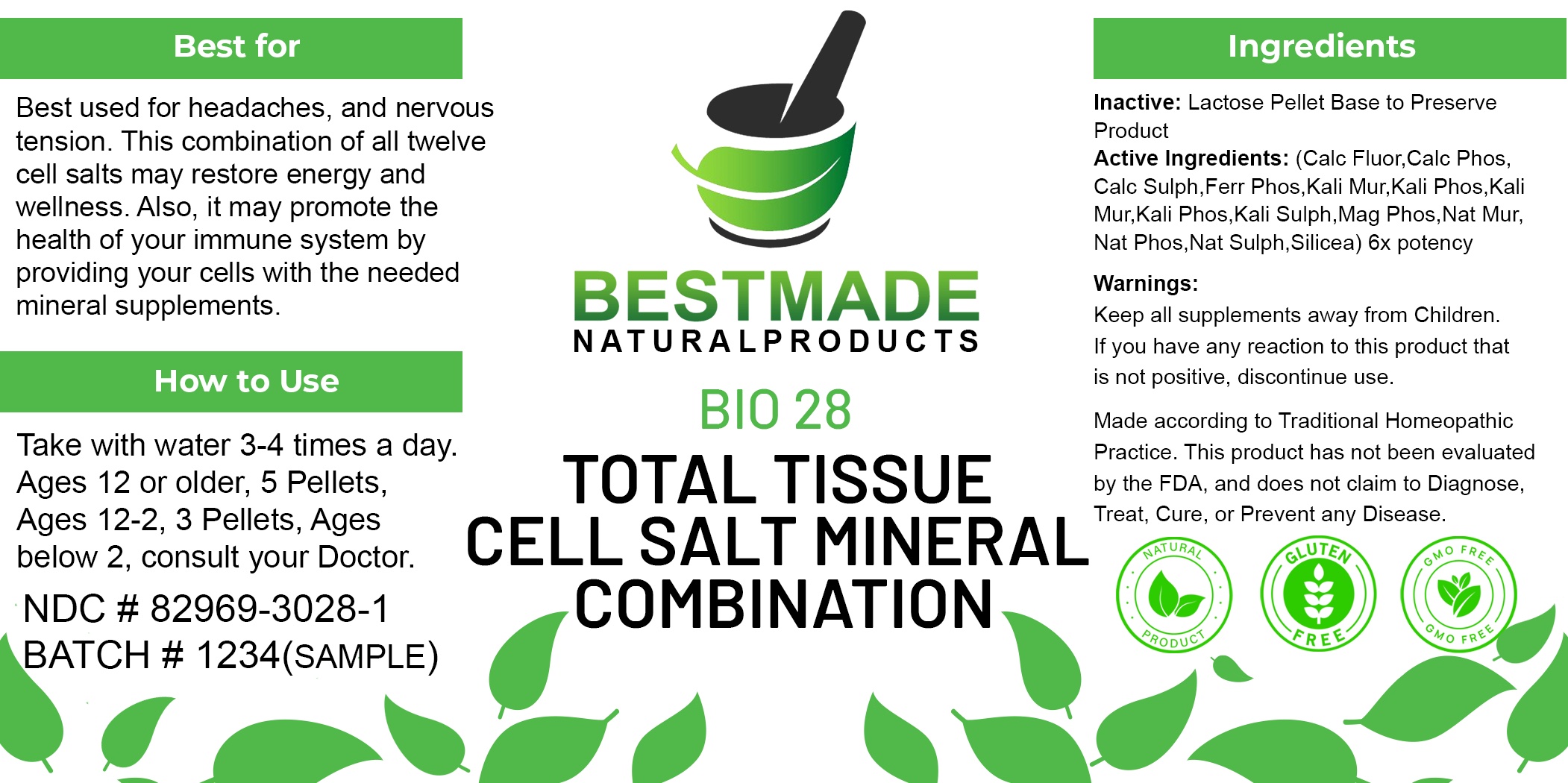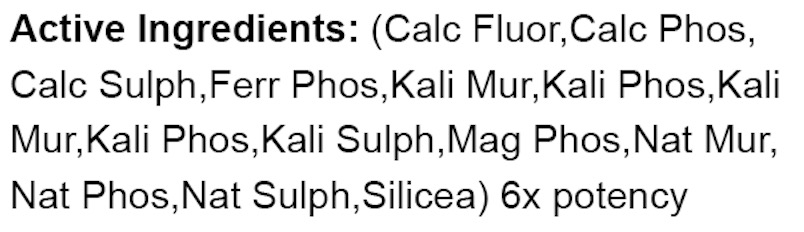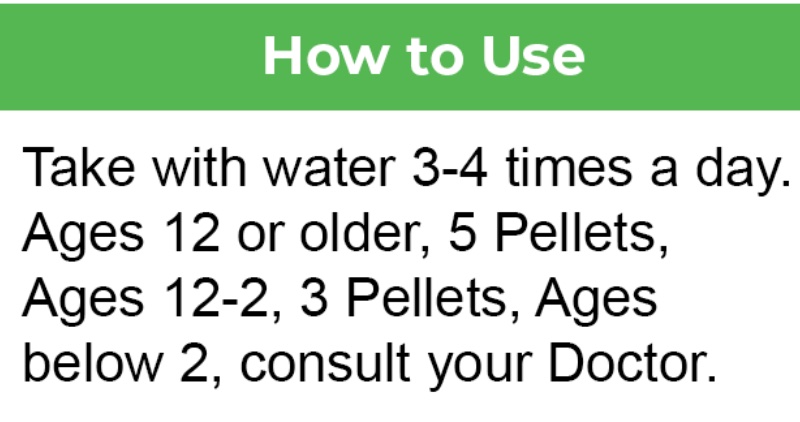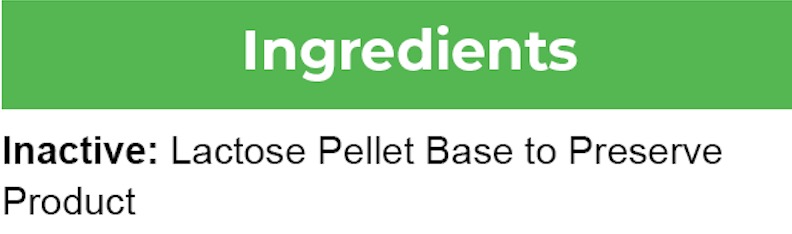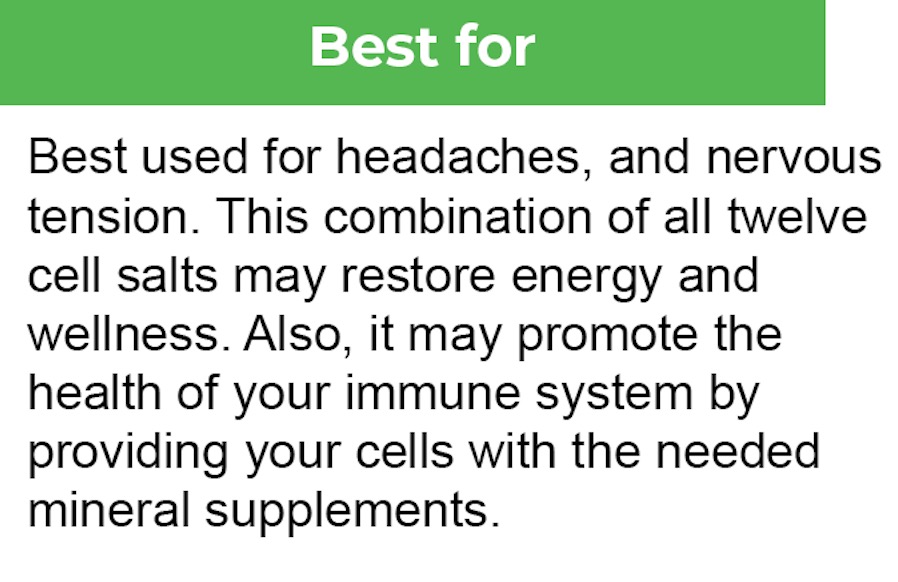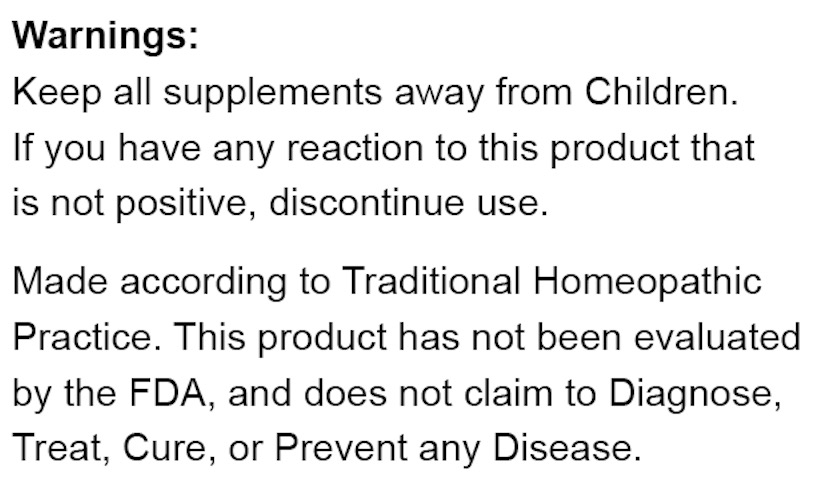 DRUG LABEL: Bestmade Natural Products Bio28
NDC: 82969-3028 | Form: TABLET, SOLUBLE
Manufacturer: Bestmade Natural Products
Category: homeopathic | Type: HUMAN OTC DRUG LABEL
Date: 20241219

ACTIVE INGREDIENTS: CALCIUM PHOSPHATE 6 [hp_X]/6 [hp_X]; CALCIUM SULFATE 6 [hp_X]/6 [hp_X]; POTASSIUM CHLORIDE 6 [hp_X]/6 [hp_X]; SODIUM SULFATE 6 [hp_X]/6 [hp_X]; FERRIC PYROPHOSPHATE 6 [hp_X]/6 [hp_X]; POTASSIUM PHOSPHATE, UNSPECIFIED FORM 6 [hp_X]/6 [hp_X]; POTASSIUM SULFATE 6 [hp_X]/6 [hp_X]; SODIUM PHOSPHATE, DIBASIC, HEPTAHYDRATE 6 [hp_X]/6 [hp_X]; MAGNESIUM PHOSPHATE, DIBASIC TRIHYDRATE 6 [hp_X]/6 [hp_X]; SODIUM CHLORIDE 6 [hp_X]/6 [hp_X]; SILICON DIOXIDE 6 [hp_X]/6 [hp_X]; CALCIUM FLUORIDE 6 [hp_X]/6 [hp_X]
INACTIVE INGREDIENTS: LACTOSE, UNSPECIFIED FORM 6 [hp_X]/6 [hp_X]

bio28

DOSAGE AND ADMINISTRATION

How to Use
Take with water 3-4 times a day.
Ages 12 or older, 5 Pellets,
Ages 12-2, 3 Pellets, Ages
below 2, consult your Doctor.

INDICATIONS AND USAGE

Best used for headaches and nervous tension. This combination of all twelve cell salts may restore energy and wellness. Also, it may promote the health of your immune system by providing your cells with the needed mineral supplements.

INACTIVE INGREDIENT

Using a blank lactose pellet base to preserve and package product.

ACTIVE INGREDIENTS
Calc Fluor, Calc Phos, Calc Sulph, Ferr Phos, Kali Mur, Kali Phos, Kali Sulph, Mag Phos, Nat Mur, Nat Phos, Nat Sulph, Silicea)6x

Keep out of reach of children.

PURPOSE

purpose: Best used for headaches and nervous tension. This combination of all twelve cell salts may restore energy and wellness. Also, it may promote the health of your immune system by providing your cells with the needed mineral supplements.

Warnings:
Keep all supplements away from Children.
If you have any reaction to this product that is not positive, discontinue use.

Made according to Traditional Homeopathic Practice. This product has not been evaluated by the FDA, and does not claim to Diagnose, Treat, Cure, or Prevent any Disease.

RECENT MAJOR CHANGES

Package label redesigned.

bio28

Entire Package Label